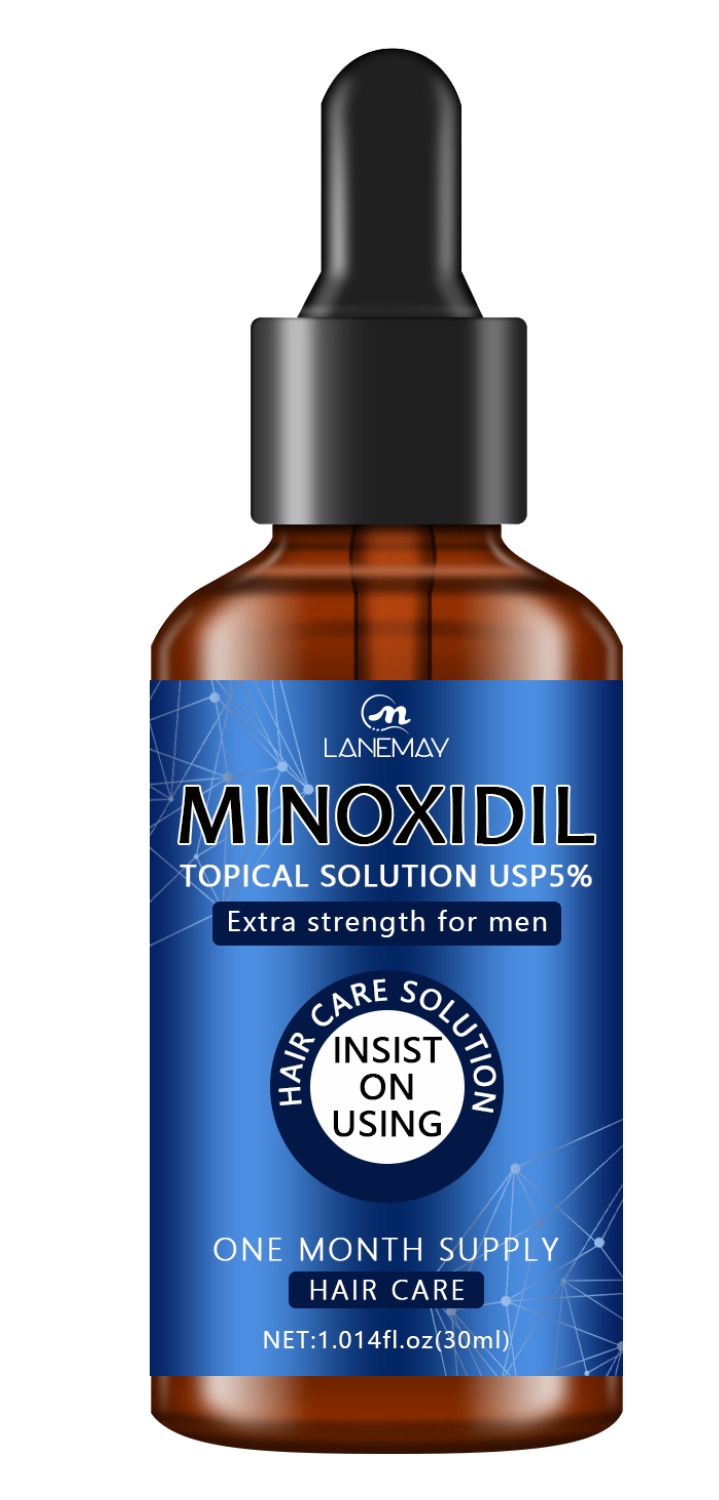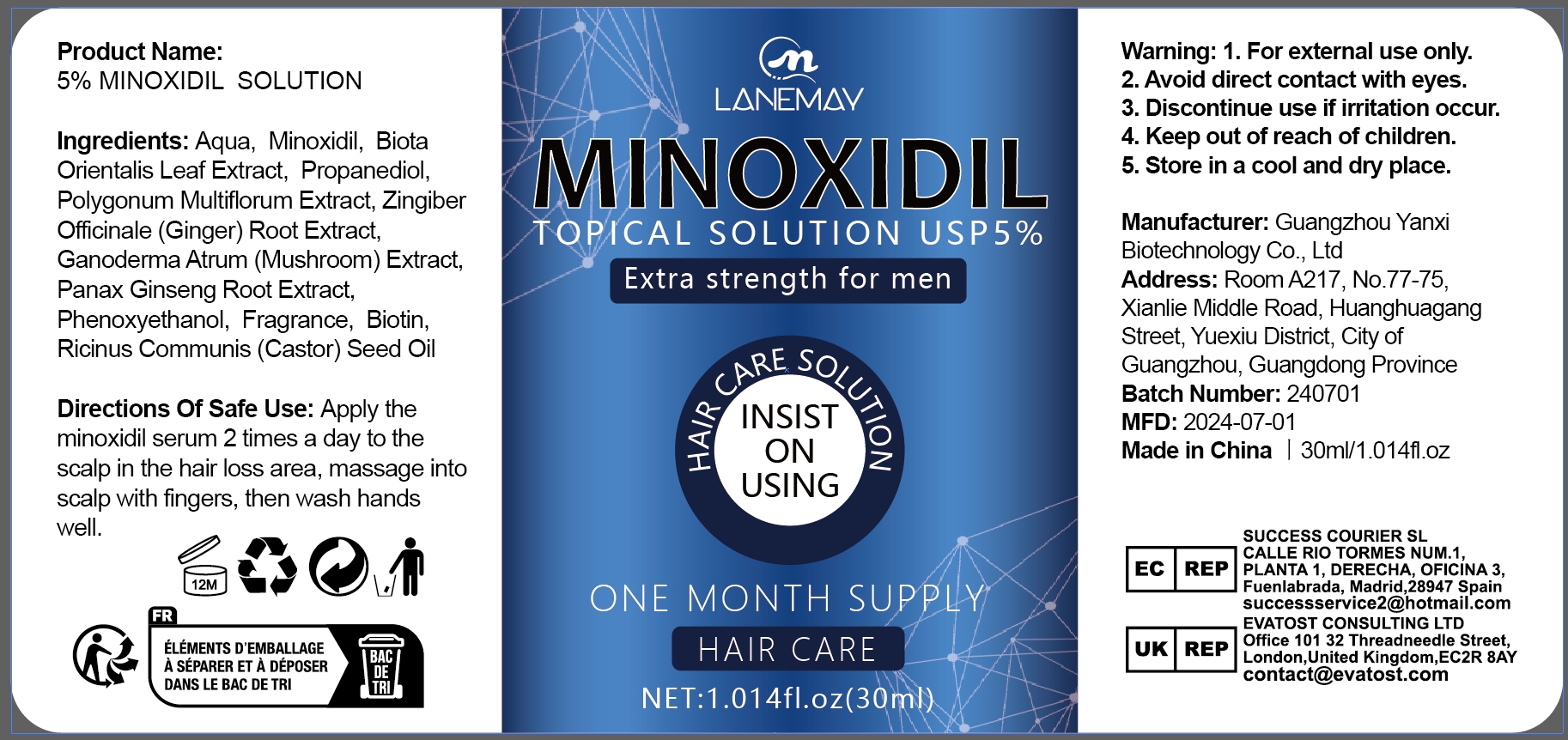 DRUG LABEL: 5% MINOXIDILSOLUTION
NDC: 84025-179 | Form: LIQUID
Manufacturer: Guangzhou Yanxi Biotechnology Co.. Ltd
Category: otc | Type: HUMAN OTC DRUG LABEL
Date: 20240904

ACTIVE INGREDIENTS: MINOXIDIL 3 mg/30 mL; PROPANEDIOL 5 mg/30 mL
INACTIVE INGREDIENTS: WATER

DOSAGE AND ADMINISTRATION

Hair growth solution for treating male hair loss

WARNINGS

keep out of children

INACTIVE INGREDIENT

AQUA

INDICATIONS AND USAGE

For daily hair care

keep out of children

PURPOSE

Promote hair growth and relieve hair loss